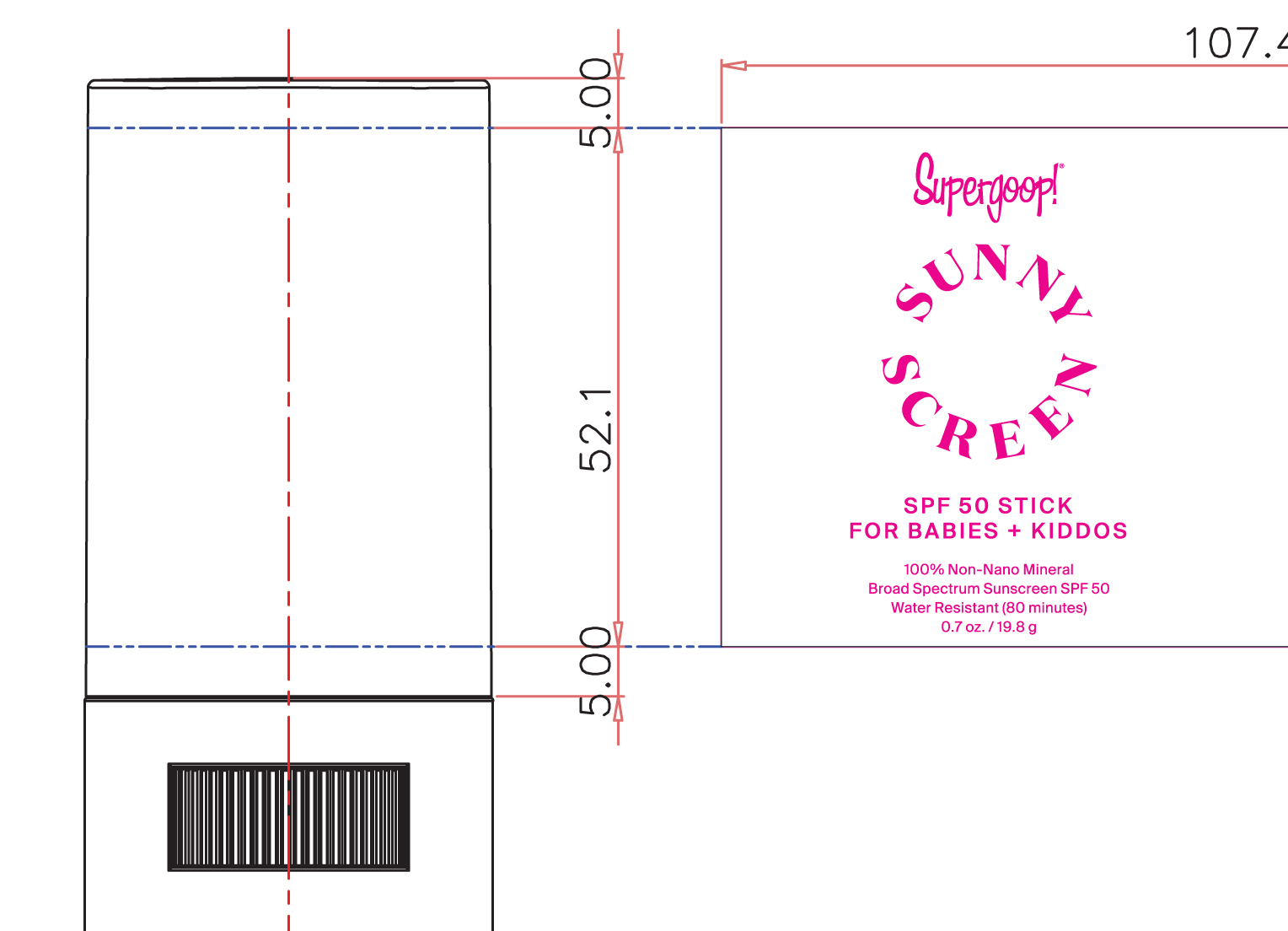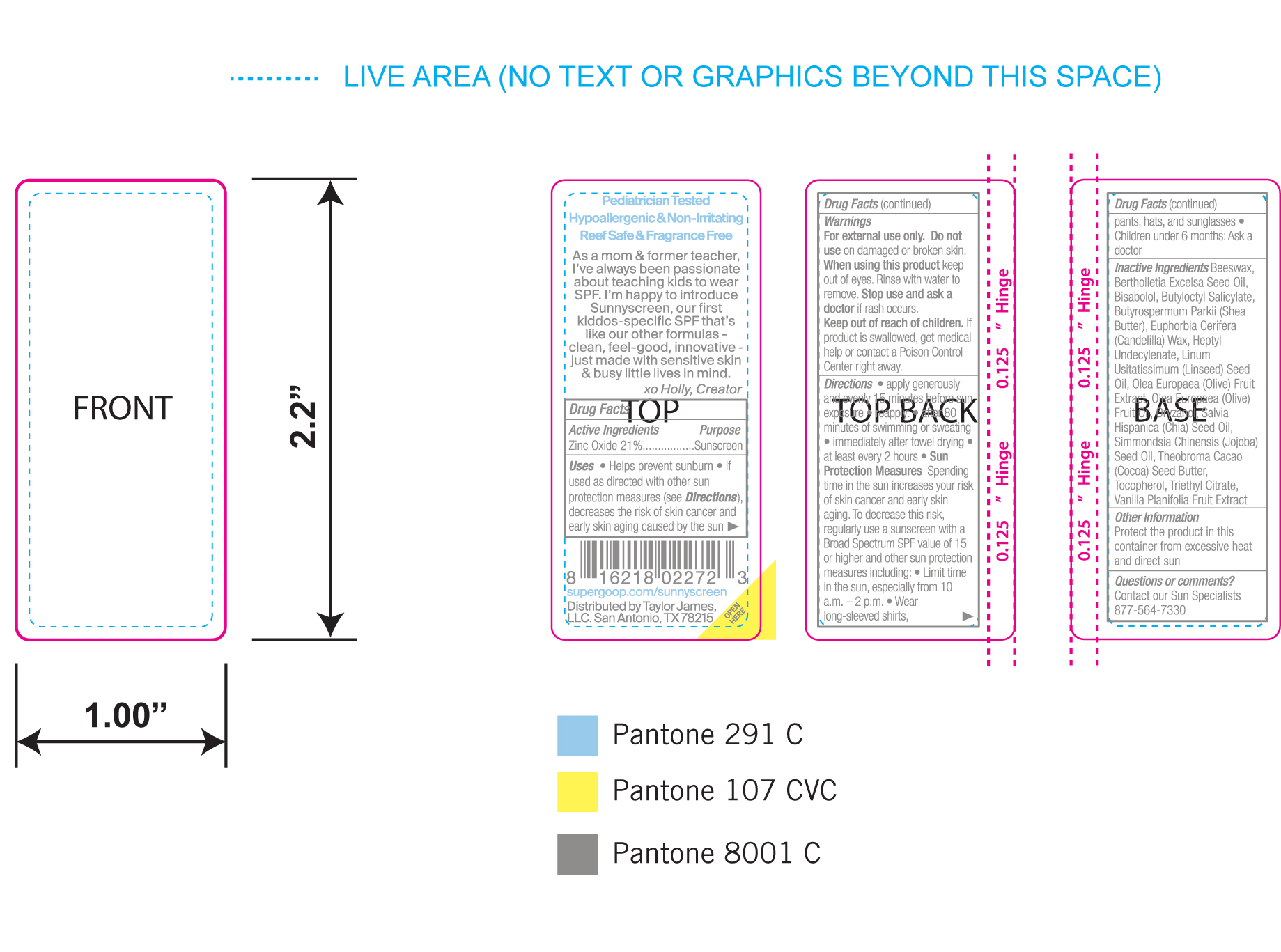 DRUG LABEL: Sunnyscreen SPF 50 Stick
NDC: 75936-251 | Form: STICK
Manufacturer: Supergoop, LLC
Category: otc | Type: HUMAN OTC DRUG LABEL
Date: 20241216

ACTIVE INGREDIENTS: ZINC OXIDE 21 g/100 g
INACTIVE INGREDIENTS: JOJOBA OIL; COCOA BUTTER; TRIETHYL CITRATE; CHIA SEED OIL; YELLOW WAX; SHEA BUTTER; ORYZANOL; HEPTYL UNDECYLENATE; LEVOMENOL; BUTYLOCTYL SALICYLATE; CANDELILLA WAX; VANILLA; LINSEED OIL; BRAZIL NUT OIL; TOCOPHEROL; OLIVE OIL

Sunnyscreen SPF 50 Stick for babies +kiddos

Active Ingredients Purpose

Zinc Oxide 21% Sunscreen

Uses

- Helps Prevent Sunburn
- If used as directed with other sun protection measures (see Directions), decreases the risk of skin cancer and early skin aging caused by the sun.

Keep out of reach of children

If product is swallowed, get medical help or contact a poison Control Center right away

Stop use and ask a doctor if rash occurs or irritation develops and lasts.

Warnings

Do not use on damaged or broken skin

When using this product keep out of eyes. Rinse with water to remove

For external use only

Directions

• Apply generously and evenly 15 minutes before sun exposure and at least
every 2 hours.

• Reapply:
• after 80 minutes of swimming or sweating • immediately after towel drying
• at least every 2 hours.
• Sun Protection Measures Spending time in the sun increases your risk of
skin cancer and early skin aging. To decrease this risk, regularly use a
sunscreen with a Broad Spectrum SPF value of 15 or higher and other sun
protection measures including: • limit your time in the sun, especially from 10
a.m. – 2 p.m.

• wear long-sleeved shirts, pants, hats, and sunglasses

• Children under 6 months of age: ask a doctor.

INACTIVE INGREDIENT

Inactive Ingredients Beeswax, Bertholletia Excelsa Seed Oil, Bisabolol, Butyloctyl Salicylate, Butyrospermum Parkii (Shea Butter), Euphorbia Cerifera (Candelilla) Wax, Heptyl Undecylenate, Linum Usitassimum (Lineseed) Oil, Olea Europaea (Olive) Fruit Extract, Olea Europaea (Olive) Fruit Oil, Oryzanol, Salvia hispanica (Chia) Seed Oil, SImmondsia Chinensis (Jojoba) Seed Oil, Theobroma Cacao(Cocoa) Seed Butter, Tocopherol, Triethyl Citrate, Vanilla Planifolia Fruit Extract

PACKAGE LABEL

Sunnyscreen

SPF 50 Stick for babies + kiddos

Broad Spectrum Sunscreen SPF 50

Water Resistant (80 minutes)

0.7 oz. / 19.8g